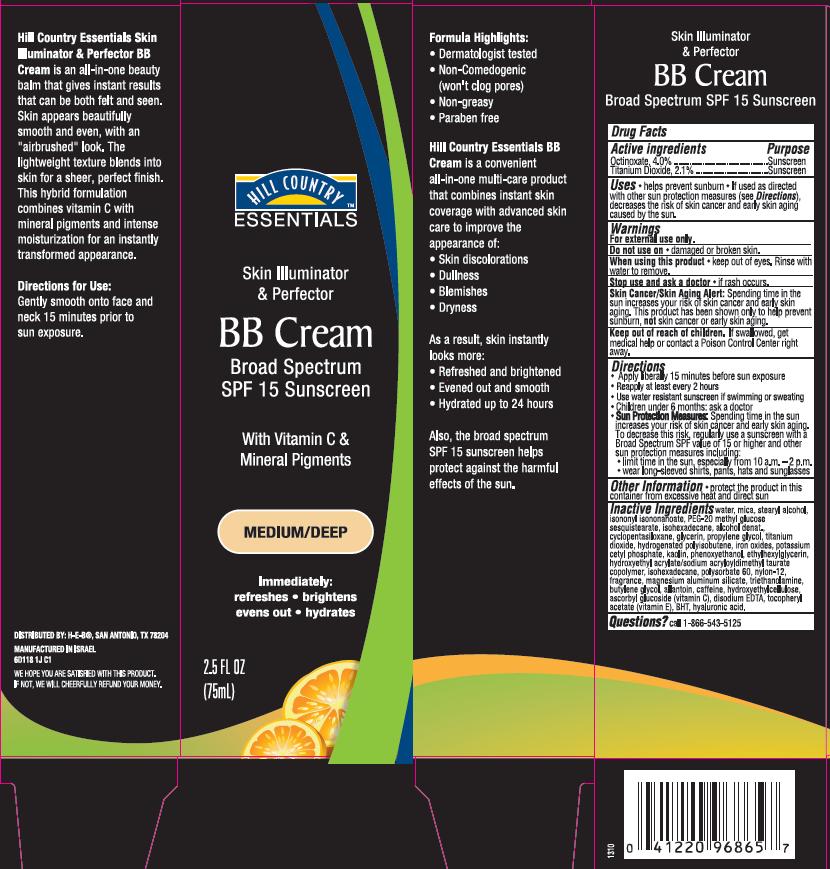 DRUG LABEL: H-E-B Skin Corrective Innovative Skin Perfector BB Broad Spectrum SPF15 Sunscreen Medium/Deep
NDC: 42421-618 | Form: CREAM
Manufacturer: Emilia Personal Care Inc.
Category: otc | Type: HUMAN OTC DRUG LABEL
Date: 20140109

ACTIVE INGREDIENTS: TITANIUM DIOXIDE 2.1 g/100 mL; OCTINOXATE 4 g/100 mL
INACTIVE INGREDIENTS: WATER; MICA; STEARYL ALCOHOL; ISONONYL ISONONANOATE; ISOHEXADECANE; ALCOHOL; CYCLOMETHICONE 5; GLYCERIN; PROPYLENE GLYCOL; HYDROGENATED POLYBUTENE (1300 MW); FERROUS OXIDE; POTASSIUM CETYL PHOSPHATE; KAOLIN; PHENOXYETHANOL; ETHYLHEXYLGLYCERIN; HYDROXYETHYL ACRYLATE/SODIUM ACRYLOYLDIMETHYL TAURATE COPOLYMER (45000 MPA.S AT 1%); POLYSORBATE 60; NYLON-12; MAGNESIUM ALUMINUM SILICATE; TROLAMINE; BUTYLENE GLYCOL; ALLANTOIN; CAFFEINE; HYDROXYETHYL CELLULOSE (5500 MPA.S AT 2%); ASCORBYL GLUCOSIDE; EDETATE DISODIUM; .ALPHA.-TOCOPHEROL ACETATE; BUTYLATED HYDROXYTOLUENE; HYALURONIC ACID

Hill Country Essentials Skin Illuminator & Perfector BB Cream

Active ingredient

Octinoxate, 4.0%
Titanium Dioxide, 2.1%

Purpose

Sunscreen

Uses

- helps prevent sunburn

If used as directed with other sun protection measures (see Directions), decreases the risk of skin cancer and early skin aging caused by the sun.

Warnings

For external use only.

Do not use on

damaged or broken skin.

When using this product

keep out of eyes. Rinse with water to remove.

Stop use and ask a doctor

if rash occurs.

Skin Cancer/Skin Aging Alert:

Spending time in the sun increases your risk of skin cancer and early skin aging. This product has been shown only to help prevent sunburn, not skin cancer or early skin aging.

Keep Out of Reach of Children

If swallowed, get medical help or contact a Poison Control Center right away.

Directions

- Apply liberally 15 minutes before sun exposure
- Reapply at least every 2 hours
- Use water resistant sunscreen if swimming or sweating
- Children under 6 months: ask a doctor
- Sun Protection Measures: Spending time in the sun increases your risk of skin cancer and early skin aging. To decrease this risk, regularly use a sunscreen with a Broad Spectrum SPF value of 15 or higher and other sun protection measures including:
  - limit time in the sun, especially from 10 a.m. – 2 p.m.
  - wear long-sleeved shirts, pants, hats and sunglasses

Other Information

- protect the product in this container from excessive heat and direct sun

Inactive Ingredients

water, mica, stearyl alcohol, isononyl isononanoate, PEG-20 methyl glucose sesquistearate, isohexadecane, alcohol denat., cyclopentasiloxane, glycerin, propylene glycol, titanium dioxide, hydrogenated polyisobutene, iron oxides, potassium cetyl phosphate, kaolin, phenoxyethanol, ethylhexylglycerin, hydroxyethyl acrylate/sodium acryloyldimethyl taurate copolymer, polysorbate 60, nylon-12, fragrance, magnesium aluminum silicate, triethanolamine, butylene glycol, allantoin, caffeine, hydroxyethylcellulose, ascorbyl glucoside (vitamin C), disodium EDTA, tocopheryl acetate (vitamin E), BHT, hyaluronic acid

Questions?

call 1-866-543-5125

Package/Label Principal Display Panel

Hill Country Essentials
Skin Illuminator & Perfector
BB Cream
Broad Spectrum SPF 15 Sunscreen

With Vitamin C & Mineral Pigments

Medium/Deep

Immediately:
refreshes
brightens
evens out
hydrates

2.5 FL OZ (75 mL)

Formula Highlights:

- Dermatologist tested
- Non-Comedogenic (won’t clog pores)
- Non-greasy
- Paraben free

Hill Country Essentials BB Cream is a convenient all-in-one multi-care product that combines instant skin coverage with advanced skin care to improve the appearance of:

- Skin discolorations
- Dullness
- Blemishes
- Dryness

As a result, skin instantly looks more:

- Refreshed and brightened
- Evened out and smooth
- Hydrated up to 24 hours

Also the broad spectrum SPF 15 sunscreen helps protect against the harmful effects of the sun.

Hill Country Essentials Skin Illuminator & Perfector BB Cream is an all-in-one beauty balm that gives instant results that can be both felt and seen. Skin appears beautifully smooth and even, with an “airbrushed” look. The lightweight texture blends into skin for a sheer, perfect finish. This hybrid formulation combines vitamin C with mineral pigments and intense moisturization for an instantly transformed appearance.

Directions for Use:
Gently smooth onto face and neck 15 minutes prior to sun exposure.

DISTRIBUTED BY: H-E-B®, SAN ANTONIO, TX 78204

MANUFACTURED IN ISRAEL
6D118 1JC1

WE HOPE YOU ARE SATISFIED WITH THIS PRODUCT.
IF NOT, WE WILL CHEERFULLY REFUND YOUR MONEY.

Carton Label